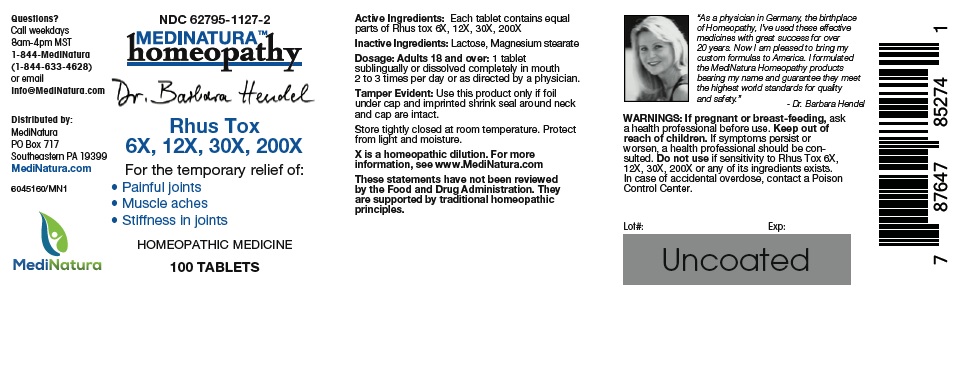 DRUG LABEL: Hendel Rhus Tox
NDC: 62795-1127 | Form: TABLET
Manufacturer: MediNatura Inc
Category: homeopathic | Type: HUMAN OTC DRUG LABEL
Date: 20220822

ACTIVE INGREDIENTS: TOXICODENDRON PUBESCENS LEAF 6 [hp_X]/1 1
INACTIVE INGREDIENTS: MAGNESIUM STEARATE; LACTOSE MONOHYDRATE

Hendel Rhus Tox

WARNINGS

If pregnant or breast-feeding, ask a health professional before use. Keep out of reach of children. If symptoms persist or worsen, a health professional should be consulted. Do not use if sensitivity to Rhus Tox 6X, 12X, 30X, 200X or any of its ingredients exists. In case of accidental overdose, contact a Poison Control Center immediately.

USES

For the temporary relief of:
• Painful Joints
• Muscle Aches
• Stiffness in Joints

KEEP OUT OF REACH OF CHILDREN

DIRECTIONS

Adults 18 and over: 1 tablet sublingually or dissolved completely in mouth 2 to 3 times per day or as directed by a physician

INDICATIONS

Painful Joints, Muscle Aches, Stiffness in Joints

INACTIVE INGREDIENT

Lactose, Magnesium stearate

INGREDIENTS

Each tablet contains equal parts of Rhus Tox 6X, 12X, 30X, 200X.

PACKAGE LABEL

Add image transcription here...